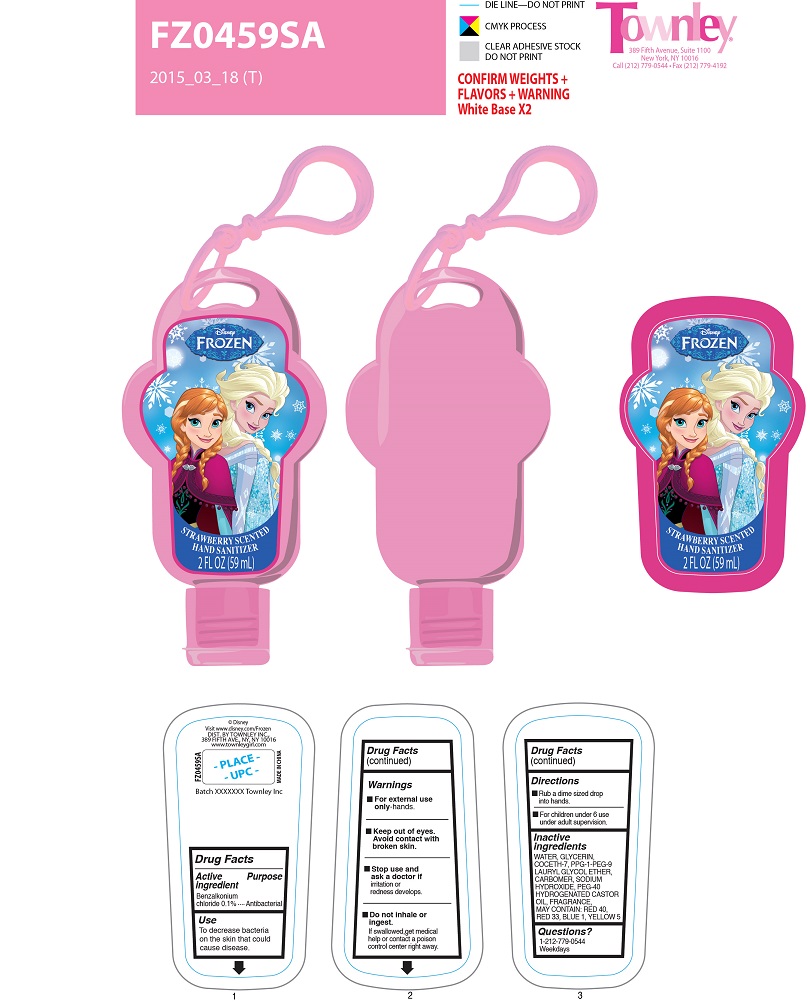 DRUG LABEL: Disney Frozen Strawberry Hand Sanitizer
NDC: 54860-022 | Form: GEL
Manufacturer: SHENZHEN LANTERN SCIENCE CO., LTD
Category: otc | Type: HUMAN OTC DRUG LABEL
Date: 20160314

ACTIVE INGREDIENTS: BENZALKONIUM CHLORIDE 1 mg/100 mg
INACTIVE INGREDIENTS: COCETH-7; CARBOMER 1342; GLYCERIN; PPG-1-PEG-9 LAURYL GLYCOL ETHER; SODIUM HYDROXIDE; CASTOR OIL; WATER

PURPOSE

Antibacterial

To decrease bacteria on skin that could cause disease

ACTIVE INGREDIENT

BENZALKONIUM CHLORIDE.......0.1%

DOSAGE AND ADMINISTRATION

Rub a dime sized drop into hands

For children under 6 use unde adult supervision

WARNINGS

For external use only - hands

Keep out of eyes.

Avoid contact with broken skin.

Do not inhale or ingest

If swallowed get medical help or contact a poison control center right away

KEEP OUT OF REACH OF CHILDREN

For children under 6, use under adult supervision

INDICATIONS AND USAGE

To decrease bacteria on skin that could cause disease.

INACTIVE INGREDIENTS

WATER (AQUA/EAU)
GLYCERIN
COCETH-7
PPG-1-PEG-9 LAURYL GLYCOL ETHER
CARBOMER
PEG-40 HYDROGENATED CASTOR OIL
FRAGRANCE (PARFUM)
SODIUM HYDROXIDE